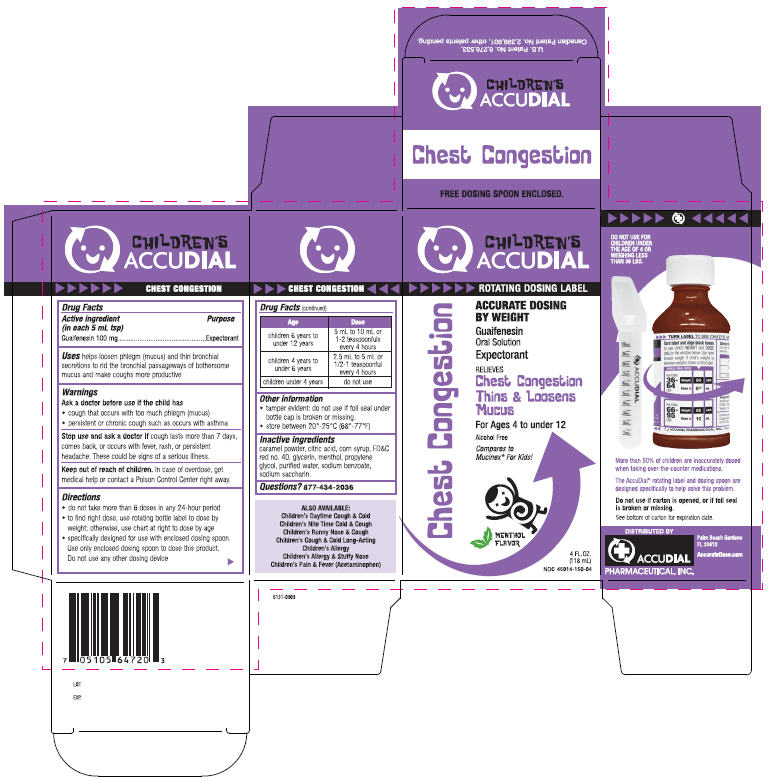 DRUG LABEL: Chest Congestion
NDC: 45014-150 | Form: LIQUID
Manufacturer: Accudial Pharmaceutical, Inc.
Category: otc | Type: HUMAN OTC DRUG LABEL
Date: 20091015

ACTIVE INGREDIENTS: Guaifenesin 100 mg/5 mL
INACTIVE INGREDIENTS: Caramel; Citric Acid Monohydrate; Corn Syrup; FD&C RED NO. 40; Glycerin; Menthol; Propylene Glycol; Water; Sodium Benzoate; Saccharin Sodium

CHILDREN'S
ACCUDIAL

CHEST CONGESTION

Drug Facts

Active ingredient (in each 5 mL tsp)

Guaifenesin 100 mg

Purpose

Expectorant

Uses

helps loosen phlegm (mucus) and thin bronchial secretions to rid the bronchial passageways of bothersome mucus and make coughs more productive

Warnings

Ask a doctor before use if the child has

- cough that occurs with too much phlegm (mucus)
- persistent or chronic cough such as occurs with asthma

Stop use and ask a doctor if cough lasts more than 7 days, comes back, or occurs with fever, rash, or persistent headache. These could be signs of a serious illness.

Keep out of reach of children. In case of overdose, get medical help or contact a Poison Control Center right away.

Directions

- do not take more than 6 doses in any 24-hour period
- to find right dose, use rotating bottle label to dose by weight; otherwise, use chart at right to dose by age
- specifically designed for use with enclosed dosing spoon. Use only enclosed dosing spoon to dose this product.
  Do not use any other device

Age | Dose
children 6 years to under 12 years | 5 mL to 10 mL or 1-2 teaspoonfuls every 4 hours
childen 4 years to under 6 years | 2.5 mL to 5 mL or 1/2-1 teaspoonful every 4 hours
children under 4 years | do not use

Other information

- tamper evident: do not use if foil seal under bottle cap is broken or missing.
- store between 20°-25°C (68°-77°F)

Inactive ingredients

caramel powder, citric acid, corn syrup, FD&C red no. 40, glycerin, menthol, propylene glycol, purified water, sodium benzoate, sodium saccharin.

Questions?

877-434-2036

PRINCIPAL DISPLAY PANEL - 118 mL Carton

CHILDREN'S
ACCUDIAL

ROTATING DOSING LABEL

ACCURATE DOSING
BY WEIGHT

Guaifenesin
Oral Solution

Expectorant

RELIEVES
Chest Congestion
Thins & Loosens
Mucus

For Ages 4 to under 12

Alcohol Free

Compares to
Mucinex® For Kids!

MENTHOL
FLAVOR

4 FL. OZ.
(118 mL)

NDC 45014-150-04

Chest Congestion